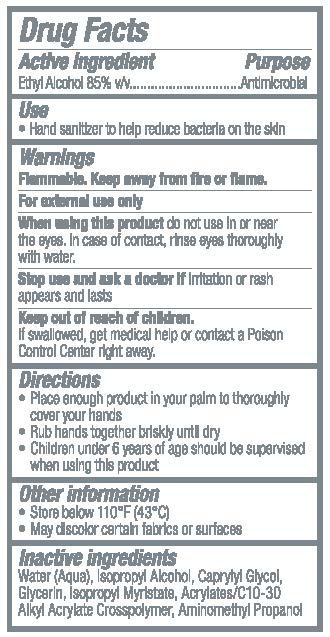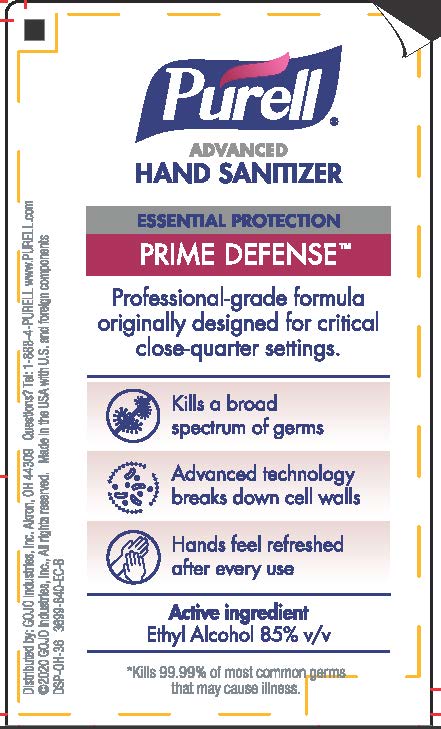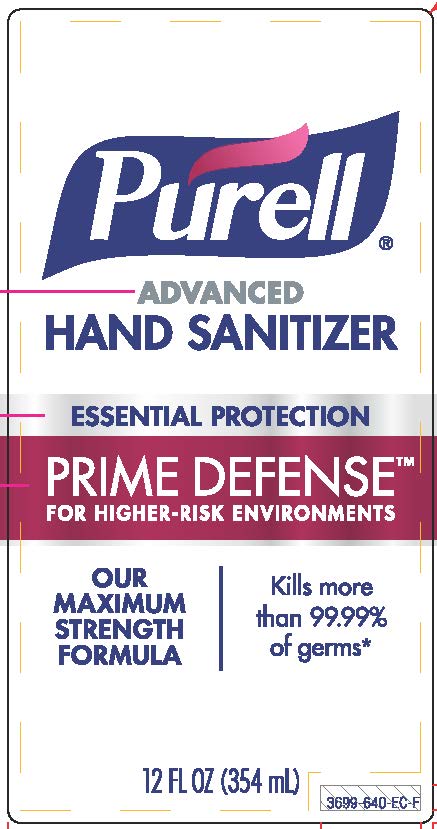 DRUG LABEL: PURELL Advanced Hand Sanitizer PRIME DEFENSE
NDC: 21749-905 | Form: GEL
Manufacturer: GOJO Industries, Inc.
Category: otc | Type: HUMAN OTC DRUG LABEL
Date: 20241216

ACTIVE INGREDIENTS: ALCOHOL 85 mL/100 mL
INACTIVE INGREDIENTS: ISOPROPYL ALCOHOL; CAPRYLYL GLYCOL; WATER; GLYCERIN; ISOPROPYL MYRISTATE; ACRYLATES/C10-30 ALKYL ACRYLATE CROSSPOLYMER (60000 MPA.S); AMINOMETHYLPROPANOL

PURELL® Advanced Hand Sanitizer PRIME DEFENSE™

Active ingredient

Ethyl alcohol 85% v/v

Purpose

Antimicrobial

Use

Hand sanitizer to help reduce bacteria on the skin

Warnings

Flammable. Keep away from fire or flame.

For external use only

WHEN USING

When using this productdo not use in or near the eyes. In case of contact, rinse eyes thoroughly with water.

Stop use and ask a doctor ifirritation or rash appears and lasts

Keep out of reach of children.If swallowed, get medical help or contact a Poison Control Center right away.

Directions

· Place enough product in your palm to thoroughly cover your hands

· Rub hands together briskly until dry

· Children under 6 years of age should be supervised when using this product.

Inactive ingredients

Water (Aqua), Isopropyl Alcohol, Caprylyl Glycol, Glycerin, Isopropyl Myristate, Acrylates/C10-30 Alkyl Acrylate Crosspolymer, Aminomethyl Propanol